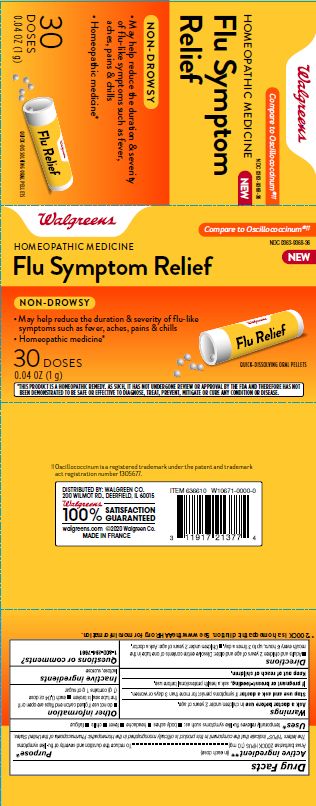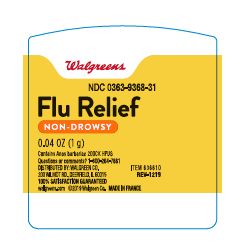 DRUG LABEL: Walgreens Flu Relief
NDC: 0363-9368 | Form: PELLET
Manufacturer: Walgreens Co.
Category: homeopathic | Type: HUMAN OTC DRUG LABEL
Date: 20231004

ACTIVE INGREDIENTS: CAIRINA MOSCHATA HEART/LIVER AUTOLYSATE 200 [kp_C]/200 [kp_C]
INACTIVE INGREDIENTS: SUCROSE; LACTOSE, UNSPECIFIED FORM

Flu Relief

ACTIVE INGREDIENT

Anas barbarie 200CK HPUS (10mg)**

PURPOSE

Anas barbarie ...... To reduce the duration and severity of flu-like symptoms

INDICATIONS AND USAGE

Temporarily relieves flu-like symptoms such as: body aches, headache, fever, chills, fatigue

Ask a doctor before use in children under 2 years of age.

Stop use and ask a doctor if symptoms persist for more than 3 days or worsen.

PREGNANCY OR BREAST FEEDING

If pregnant or breast feeding, ask a health professional before use.

Keep out of reach of children.

DOSAGE AND ADMINISTRATION

Adults and children 2 years of age and older: Dissolve entire contents of one tube in the mouth every 6 hours, up to 3 times a day. Children under 2 years of age: Ask a doctor.

Do not use if glued carton and flaps are open or if the tube seal is broken.

Each 0.04 oz. dose (1 g) contains 1 g of sugar

Dissolvable oral pellets

Contains 30 Doses
** 200CK is a homeopathic dilution. See www.theaahp.org for more information.

Non-drowsy

Homeopathic Medicine*

*This product is a homeopathic remedy, as such, it has not undergone review or approval by the FDA and therefore has not been demonstrated to be safe or effective to diagnose, treate, prevent, mitigate or cure any condition or disease.

††Oscillococcinum is a registered trademark under the patent and trademark act registration number 1305677.

INACTIVE INGREDIENT

Lactose, sucrose

QUESTIONS

1-800-264-7661